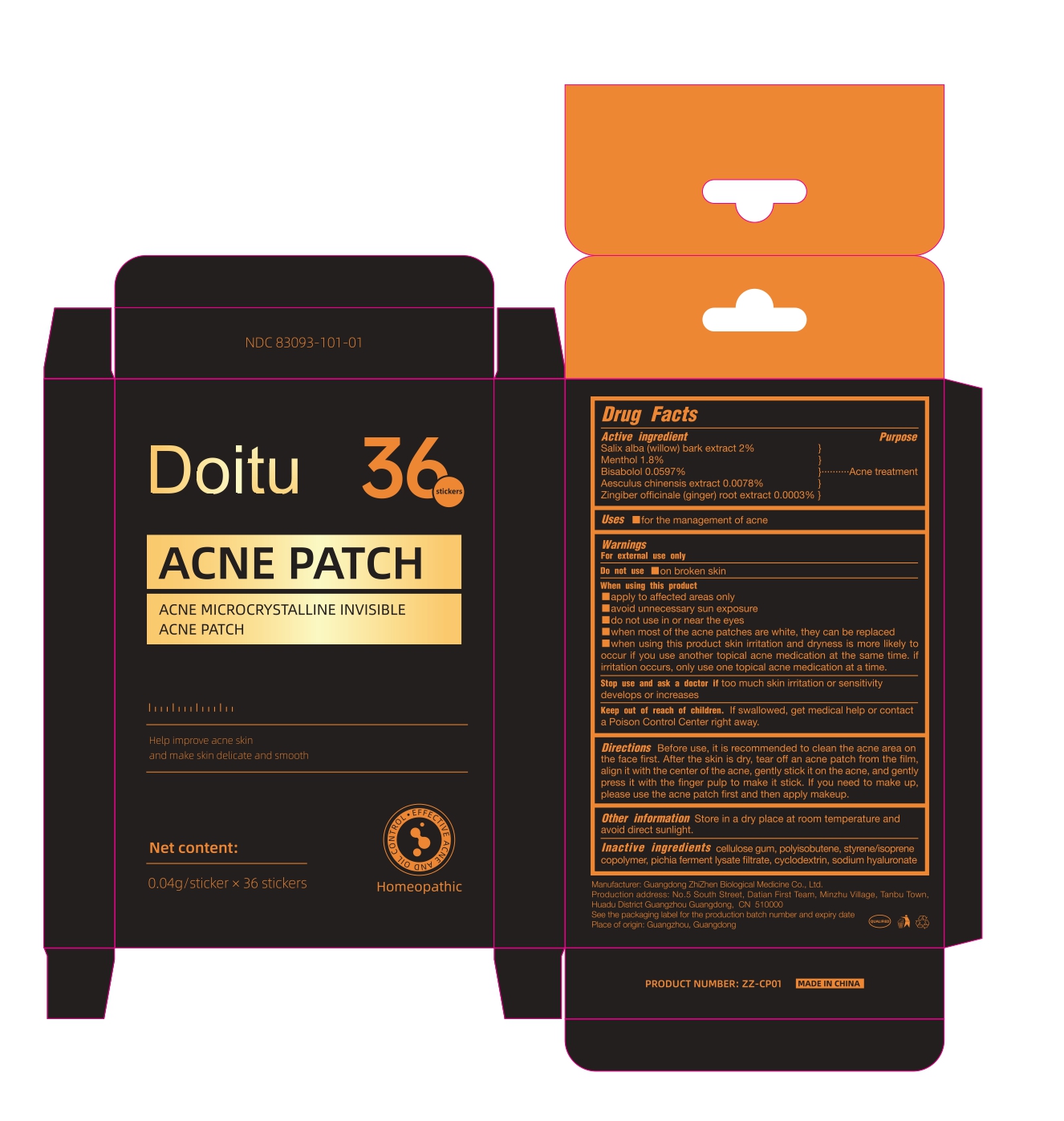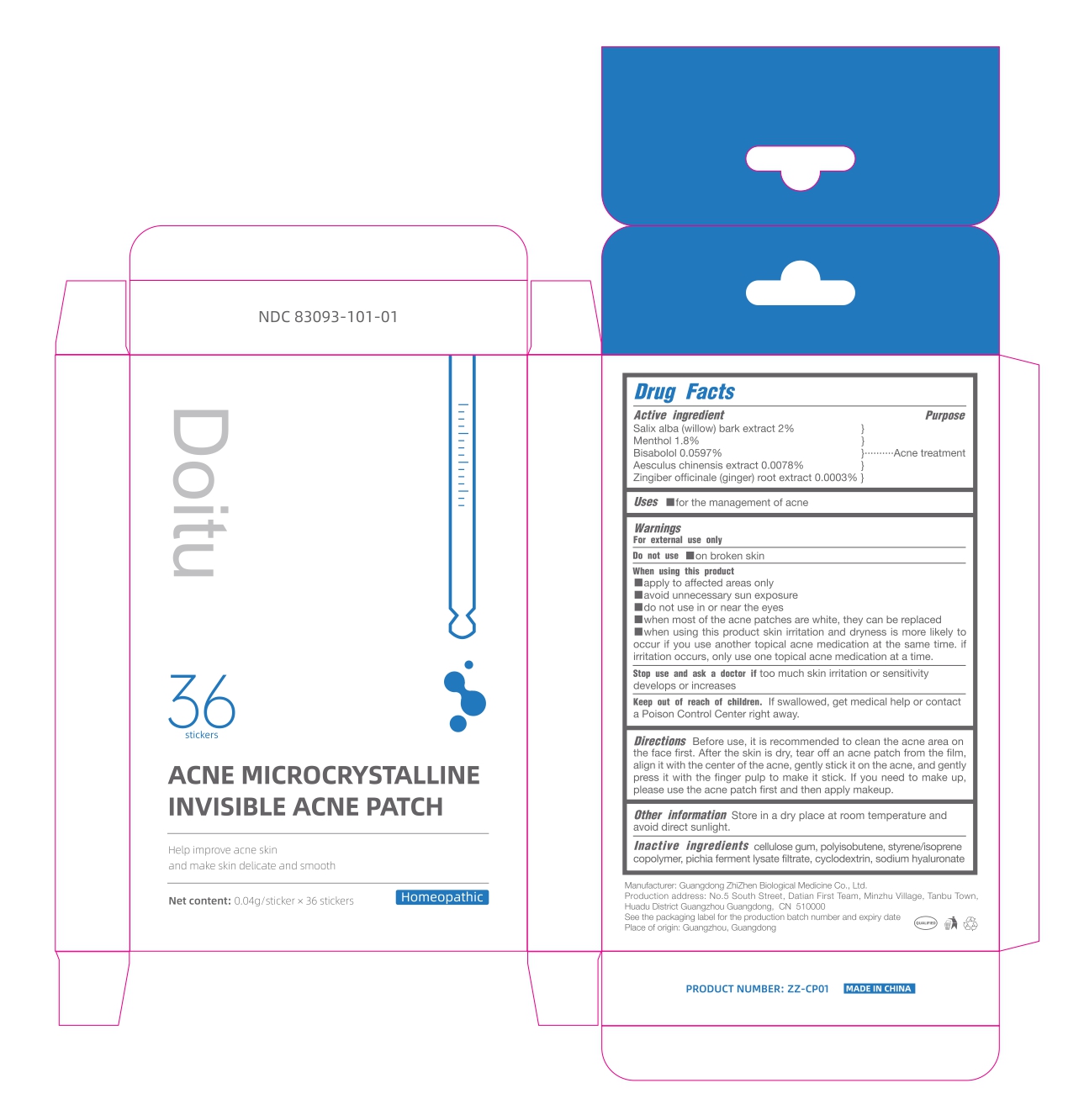 DRUG LABEL: Doitu acne microcrystalline invisible acne patch
NDC: 83093-101 | Form: PATCH
Manufacturer: Guangdong ZhiZhen Biological Medicine Co., Ltd.
Category: homeopathic | Type: HUMAN OTC DRUG LABEL
Date: 20221125

ACTIVE INGREDIENTS: SALIX ALBA BARK 0.8 mg/40 mg; GINGER 0.00012 mg/40 mg; LEVOMENOL 0.02388 mg/40 mg; MENTHOL 0.72 mg/40 mg; AESCULUS CHINENSIS WHOLE 0.00312 mg/40 mg
INACTIVE INGREDIENTS: CYCLODEXTRINS 0.04488 mg/40 mg; HYALURONATE SODIUM 0.008 mg/40 mg; POLYISOBUTYLENE (1000 MW) 15.12 mg/40 mg; PICHIA JADINII 0.6 mg/40 mg; CARBOXYMETHYLCELLULOSE SODIUM, UNSPECIFIED FORM 17.01 mg/40 mg; STYRENE/ISOPRENE/STYRENE BLOCK COPOLYMER 5.67 mg/40 mg

ACTIVE INGREDIENT

SALIX ALBA (WILLOW) BARK EXTRACT 2%

MENTHOL 1.8%

BISABOLOL 0.0597%

AESCULUS CHINENSIS EXTRACT 0.0078%

ZINGIBER OFFICINALE (GINGER) ROOT EXTRACT 0.0003%

PURPOSE

Acne treatment

WARNINGS

For external use only

WHEN USING

■Apply to affected areas only

■Avoid unnecessary sun exposure

■Do not use in or near the eyes

■When most of the acne patches are white, they can be replaced

■When using this product skin irritation and dryness is more likely to occur if you use another topical acne medication at the same time. If irritation occurs, only use one topical acne medication at a time.

Stop use and ask a doctor if too much skin irritation or sensitivity develops or increases.

Keep out of reach of children. If swallowed, get medical help or contact a Poison Control Center right away.

Directions

Before use, it is recommended to clean the acne area on the face first. After the skin is dry, tear off an acne patch from the film, align it with the center of the acne, gently stick it on the acne, and gently press it with the finger pulp to make it stick. If you need to make up, please use the acne patch first and then apply makeup.

DOSAGE AND ADMINISTRATION

Use as needed until acne subsides.

OTHER SAFETY INFORMATION

Store in a dry place at room temperature and avoid direct sunlight.

INACTIVE INGREDIENT

CELLULOSE GUM, POLYISOBUTENE, STYRENE/ISOPRENE COPOLYMER, PICHIA FERMENT LYSATE FILTRATE, CYCLODEXTRIN, SODIUM HYALURONATE